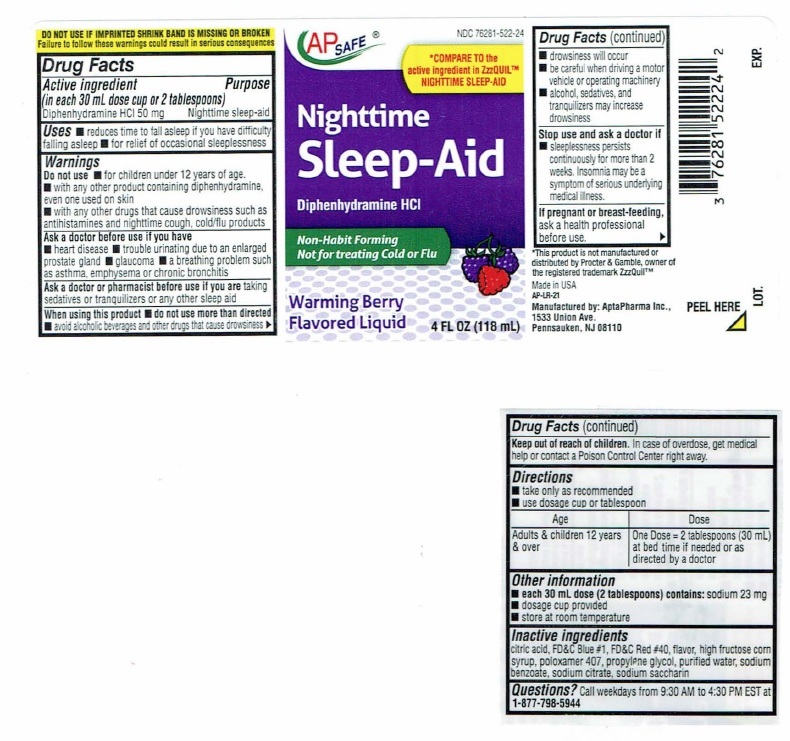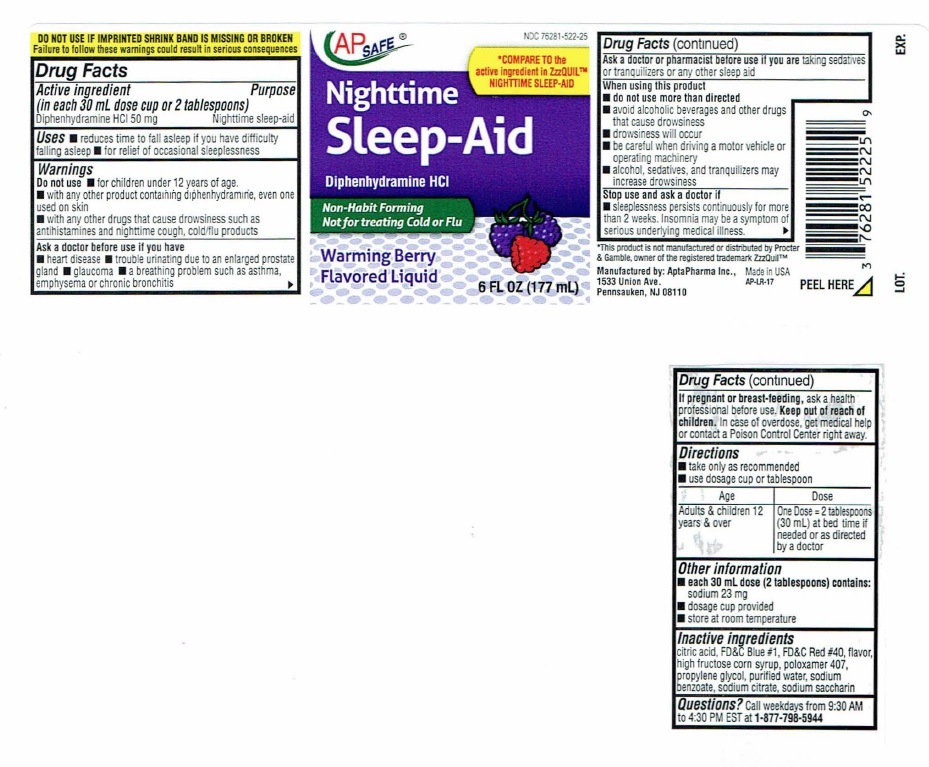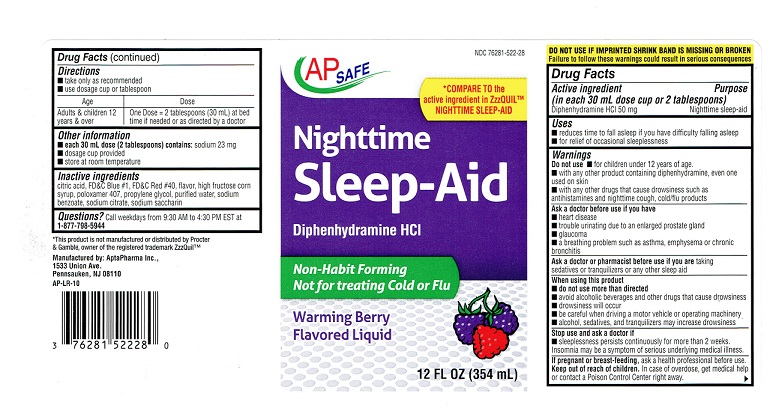 DRUG LABEL: Nighttime Sleep-Aid
NDC: 76281-522 | Form: LIQUID
Manufacturer: AptaPharma Inc.
Category: otc | Type: HUMAN OTC DRUG LABEL
Date: 20231230

ACTIVE INGREDIENTS: DIPHENHYDRAMINE HYDROCHLORIDE 50 mg/30 mL
INACTIVE INGREDIENTS: CITRIC ACID MONOHYDRATE; FD&C BLUE NO. 1; FD&C RED NO. 40; HIGH FRUCTOSE CORN SYRUP; POLOXAMER 407; PROPYLENE GLYCOL; WATER; SODIUM BENZOATE; SODIUM CITRATE; SACCHARIN SODIUM

Nighttime Sleep-Aid

Drug Facts

Active ingredient

(in each 30 mL dose cup or 2 tablespoons)
Diphenhydramine HCI 50 mg

Purpose

Nighttime sleep-aid

Uses

■ reduces time to fall asleep if you have difficulty falling asleep
■ for relief of occasional sleeplessness

Warnings

Do not use ■ for children under 12 years of age.
■ with any other product containing diphenhydramine, even one used on skin
■ with any other drugs that cause drowsiness such as antihistamines and nighttime cough, cold/flu products

Ask a doctor before use if you have

■ heart disease
■ trouble urinating due to enlarged prostrate gland
■ glaucoma
■ a breathing problem such as asthma, emphysema or chronic bronchitis

Ask a doctor or pharmacist before use if you are taking
sedatives or tranquilizers or any other sleep aid

When using this product

■ do not use more than directed
■ avoid alcoholic beverages and other drugs that cause drowsiness
■ drowsiness will occur
■ be careful when driving a motor vehicle or operating machinery
■ alcohol, sedatives, and tranquilizers may increase drowsiness

Stop use and ask a doctor if

■ sleeplessness persists continuously for more than 2 weeks.
Insomnia may be a symptom of serious underlying medical illness.

PREGNANCY OR BREAST FEEDING

If pregnant or breast-feeding, ask a health professional before use.

Keep out of reach of children. In case of overdose, get medical help
or contact a Poison Control Center right away.

Directions

■ take only as recommended
■ Use dosage cup or tablespoon

Age Dose
Adults & children 12 One Dose = 2 tablespoons (30 mL) at bed
years & over time if needed or as directed by a doctor

Other information

■ each 30 mL dose (2 tablespoons) contains: sodium 23 mg
■ dosage cup provided
■ store at room temperature

Inactive ingredients

citric acid, FD&C Blue #1, FD&C Red #40, flavor, high fructose corn
syrup, poloxamer 407, propylene glycol, purified water, sodium
benzoate, sodium citrate, sodium saccharin

QUESTIONS

Questions? Call weekdays from 9:30 AM to 4:30 PM EST at
1-877-798-5944

Nighttime Sleep-Aid Label

NDC 76281-522-28

AP SAFE

*COMPARE TO the
active ingredient in ZzzQUIL™
NIGHTTIME SLEEP-AID

Nighttime
Sleep-Aid

Diphenhydramine HCI

Non-Habit Forming
Not for treating Cold or Flu

Warming Berry
Flavored Liquid

12 FL OZ (354 mL)

DO NOTUSE IF IMPRINTEDSHRINK BAND IS MISSING OR BROKEN
Failure to follow these warnings could result in serious consequences

Drug Facts

Active ingredient Purpose
(in each 30 mL dose cup or 2 tablespoons)
Diphenhydramine HCI 50 mg…………………………Nighttime sleep-aid

Uses
■ reduces time to fall asleep if you have difficulty falling asleep
■ for relief of occasional sleeplessness

Warnings
Do not use ■ for children under 12 years of age.
■ with any other product containing diphenhydramine, even one
used on skin
■ with any other drugs that cause drowsiness such as
antihistamines and nighttime cough, cold/flu products

Ask a doctor before use if you have
■ heart disease
■ trouble urinating due to enlarged prostrate gland
■ glaucoma
■ a breathing problem such as asthma, emphysema or chronic
bronchitis

Ask a doctor or pharmacist before use if you are taking
sedatives or tranquilizers or any other sleep aid

When using this product
■ do not use more than directed
■ avoid alcoholic beverages and other drugs that cause drowsiness
■ drowsiness will occur
■ be careful when driving a motor vehicle or operating machinery
■ alcohol, sedatives, and tranquilizers may increase drowsiness

Stop use and ask a doctor if
■ sleeplessness persists continuously for more than 2 weeks.
Insomnia may be a symptom of serious underlying medical illness.

If pregnant or breast-feeding, ask a health professional before use.

Keep out of reach of children. In case of overdose, get medical help
or contact a Poison Control Center right away. ►

Drug Facts(continued)

Directions
■ take only as recommended
■ Use dosage cup or tablespoon

Age Dose
Adults & children 12 One Dose = 2 tablespoons (30 mL) at bed
years & over time if needed or as directed by a doctor

Other information
■ each 30 mL dose (2 tablespoons) contains: sodium 23 mg
■ dosage cup provided
■ store at room temperature

Inactive ingredients
citric acid, FD&C Blue #1, FD&C Red #40, flavor, high fructose corn
syrup, poloxamer 407, propylene glycol, purified water, sodium
benzoate, sodium citrate, sodium saccharin

Questions? Call weekdays from 9:30 AM to 4:30 PM EST at
1-877-798-5944

*This product is not manufactured or distributed by Procter
& Gamble, owner of the registered trademark ZzzQuil™

Manufactured by: AptaPharma Inc.,
1533 Union Ave.,
Pennsauken, NJ 08110

AP-LR-10

6 OZ

4 OZ

res